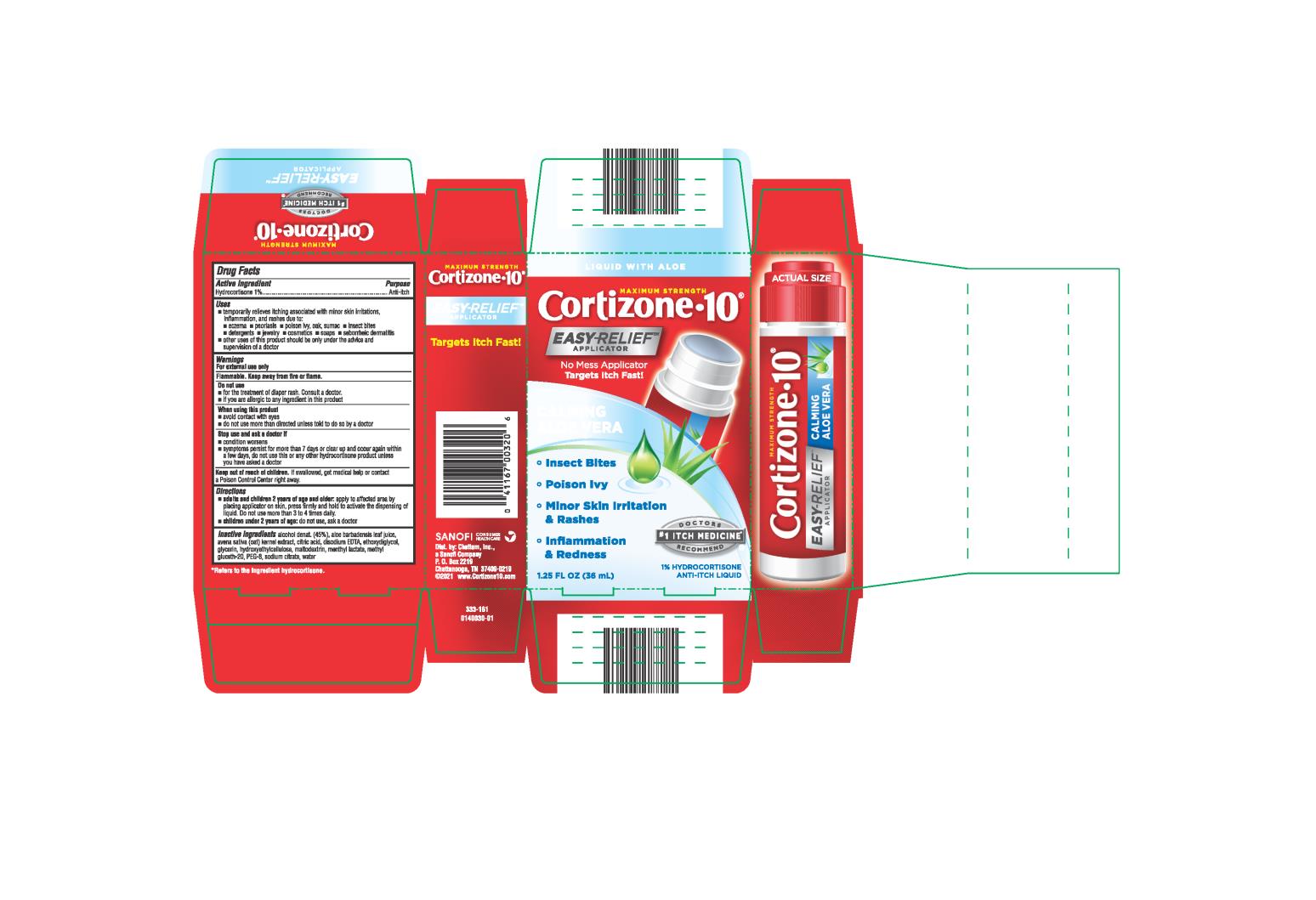 DRUG LABEL: Cortizone 10 Easy Relief
NDC: 41167-0032 | Form: LIQUID
Manufacturer: Chattem, Inc.
Category: otc | Type: HUMAN OTC DRUG LABEL
Date: 20231025

ACTIVE INGREDIENTS: HYDROCORTISONE 10 mg/1 mL
INACTIVE INGREDIENTS: ALOE VERA LEAF; OAT; CITRIC ACID MONOHYDRATE; EDETATE DISODIUM; DIETHYLENE GLYCOL MONOETHYL ETHER; POLYETHYLENE GLYCOL 400; GLYCERIN; HYDROXYETHYL CELLULOSE, UNSPECIFIED; MALTODEXTRIN; MENTHYL LACTATE, (-)-; ALCOHOL; METHYL GLUCETH-20; SODIUM CITRATE; WATER

Cortizone 10 Easy Relief

Cortizone-10® Easy Relief Applicator

Active Ingredient:

Hydrocortisone 1%

Purpose

Anti-itch

Uses

- temporarily relieves itching associated with minor skin irritations, inflammation, and rashes due to:
  • eczema
  • psoriasis
  • poison ivy, oak, sumac
  • insect bites
  • detergents
  • jewelry
  • cosmetics
  • soaps
  • seborrheic dermatitis
- other uses of this product should be only under the advice and supervision of a doctor

Warnings

For external use only

Flammable. Keep away from fire or flame.

Do not use

- for the treatment of diaper rash. Consult a doctor.
- if you are allergic to any ingredient in this product

When using this product

- avoid contact with eyes
- do not use more than directed unless told to do so by a doctor.

Stop use and ask a doctor if

- condition worsens
- symptoms persist for more than 7 days or clear up and occur again within a few days, do not use this or any other hydrocortisone product unless you have asked a doctor

Keep out of reach of children.

If swallowed, get medical help or contact a Poison Control Center right away.

Directions

- adults and children 2 years of age and older: apply to affected area by placing applicator on skin, press firmly and hold to activate the dispensing of liquid. Do not use more than 3 to 4 times daily.
- children under 2 years of age: do not use, ask a doctor

Inactive Ingredients

Alcohol denat. (45%), aloe barbadensis leaf juice, avena sativa (oat) kernel extract, citric acid, disodium EDTA, ethoxydiglycol, glycerin, hydroxyethyl cellulose, maltodextrin, menthyl lactate, methyl gluceth-20, PEG-8, , sodium citrate, water

KEEP CARTON AS IT CONTAINS IMPORTANT INFORMATION.

Close cap tightly after use. 0042734-03

*Refers to the ingredient hydrocortisone

CHATTEM®

Distributed by: Chattem, Inc.
P.O. Box 2219, Chattanooga,TN 37409-0219
U.S.A. ©2008 www.chattem.com

Principal Display Panel

MAXIMUM STRENGTH

Cortizone●10®

EASY RELIEFTM

APPLICATOR

Targets Itch Fast!

- Insect Bites
- Redness & Inflammation
- Skin Irritation & Rashes
- No Mess

with Healing Aloe

1% HYDROCORTISONE ANTI-ITCH LIQUID

1.25 fl oz (36mL)